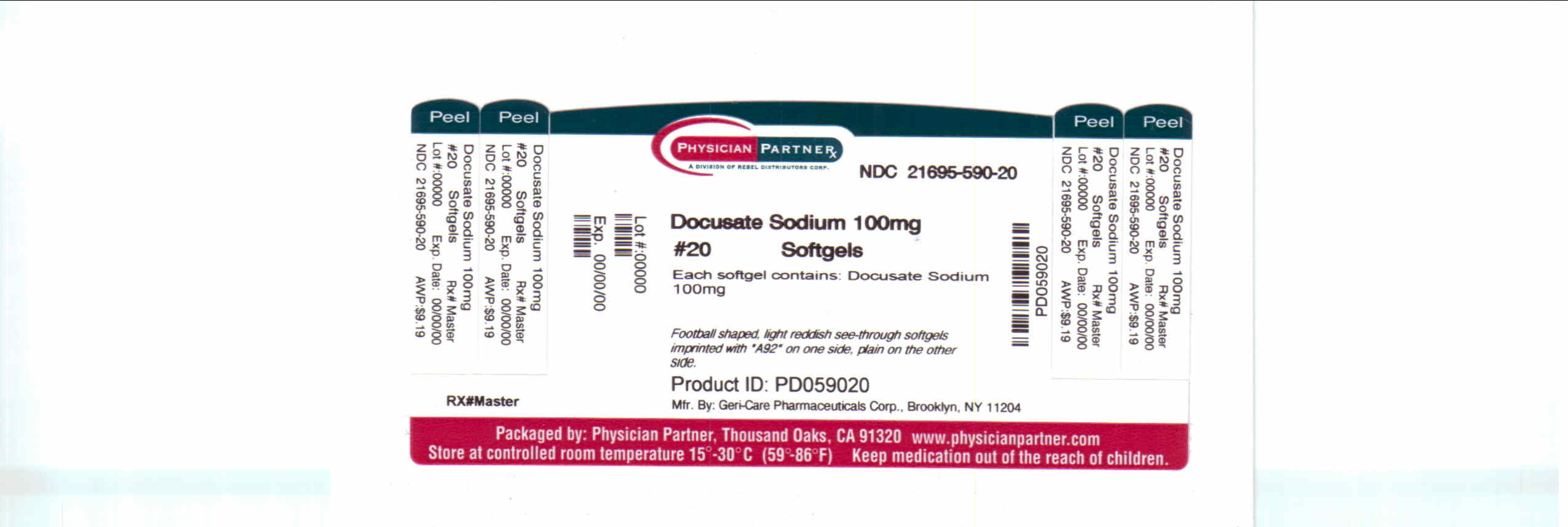 DRUG LABEL: Docusate Sodium
NDC: 21695-590 | Form: CAPSULE
Manufacturer: Rebel Distributors Corp
Category: otc | Type: HUMAN OTC DRUG LABEL
Date: 20110215

ACTIVE INGREDIENTS: DOCUSATE SODIUM 100 mg/1 1
INACTIVE INGREDIENTS: CITRIC ACID MONOHYDRATE; D&C RED NO. 33; D&C YELLOW NO. 10; ETHYL VANILLIN; FD&C BLUE NO. 1; FD&C RED NO. 40; FD&C YELLOW NO. 6; GELATIN; GLYCERIN; MANNITOL; METHYLPARABEN; POLYETHYLENE GLYCOL; PROPYLENE GLYCOL; PROPYLPARABEN; SORBITOL; WATER

Docusate Sodium Drug Facts

Active ingredient

Docusate Sodium 100mg

Purpose

Stool Softener

Keep Out of Reach of Children

In case of overdose, get medical help or contact a Poison Control center right way.

Uses

Prevents / relieves dry hard stool. Results usually occur 1 to 3 days after the first dose.

Warnings

Do not use for more than one week unless directed by a doctor.

Ask a doctor before use if you have abdominal pain, nausea, or vomiting; have noticed a sudden change in bowel habits that lasts over 2 weeks,; are taking mineral oil.

Stop use and ask a doctor if you have no bowel movement within 3 days; you have rectal bleeding. These could be signs of a serious condition.

If pregnant or breast-feeding, ask a health professional before use.

Tamper Evident: Do not use if imprinted seal under cap is missing or broken.

Directions

Adults and children 12 years and older: take 1-2 softgels daily until first bowel movement; 1 softgel daily thereafter, or as directed by a doctor.

Children under 12: consult a doctor.

Do not exceed recommended dose.

Other Information

Each softgel contains sodium 5mg.

Product from Canada or USA

Store at room temperature, 15°C-30°C (59°F-86°F)

Inactive ingredients

may contain cirtic acid, D&C red no. 33, D&C yellow no. 10, ethyl vanillin, FD&C blue no. 1, FD&C re no. 40 FD&C yellow no. 6, gelatin, glycerin, edible ink, mannitol, methylparaben, polyethylene glycol, propylene glycol, propylparaben, sorbitol, water.

Distributed by:

Geri-Care Pharmaceuticals Corp.

Brooklyn, NY 11204

Repackaged by:

Rebel Distributors Corp

Thousand Oaks, CA 91320